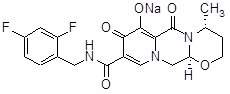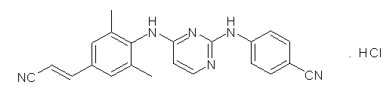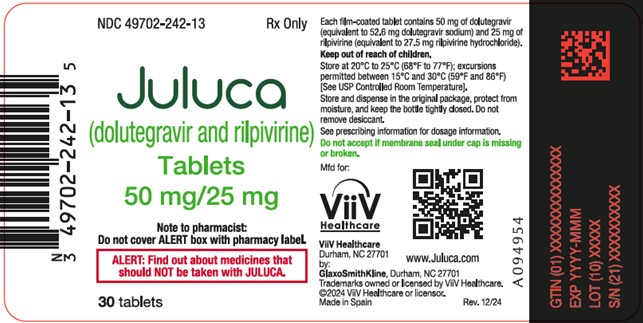 DRUG LABEL: Juluca
NDC: 49702-242 | Form: TABLET, FILM COATED
Manufacturer: ViiV Healthcare Company
Category: prescription | Type: HUMAN PRESCRIPTION DRUG LABEL
Date: 20251029

ACTIVE INGREDIENTS: DOLUTEGRAVIR SODIUM 50 mg/1 1; RILPIVIRINE HYDROCHLORIDE 25 mg/1 1
INACTIVE INGREDIENTS: CROSCARMELLOSE SODIUM; MANNITOL; LACTOSE MONOHYDRATE; MICROCRYSTALLINE CELLULOSE; POLYSORBATE 20; POVIDONE K30; SODIUM STARCH GLYCOLATE TYPE A CORN; SODIUM STEARYL FUMARATE

HIGHLIGHTS OF PRESCRIBING INFORMATION

These highlights do not include all the information needed to use JULUCA safely and effectively. See full prescribing information for JULUCA.
JULUCA (dolutegravir and rilpivirine tablets), for oral use
Initial U.S. Approval: 2017

1 INDICATIONS AND USAGE

JULUCA, a two-drug combination of dolutegravir, an HIV-1 integrase strand transfer inhibitor (INSTI), and rilpivirine, an HIV-1 non-nucleoside reverse transcriptase inhibitor (NNRTI), is indicated as a complete regimen for the treatment of HIV-1 infection in adults to replace the current antiretroviral regimen in those who are virologically suppressed (HIV-1 RNA less than 50 copies/mL) on a stable antiretroviral regimen for at least 6 months with no history of treatment failure and no known substitutions associated with resistance to the individual components of JULUCA. (1)

2 DOSAGE AND ADMINISTRATION

- One tablet taken orally once daily with a meal. (2.1)
- Rifabutin coadministration: Take an additional 25-mg tablet of rilpivirine with JULUCA once daily with a meal for the duration of the rifabutin coadministration. (2.2)

3 DOSAGE FORMS AND STRENGTHS

Each tablet contains: 50 mg of dolutegravir (equivalent to 52.6 mg dolutegravir sodium) and 25 mg of rilpivirine (equivalent to 27.5 mg rilpivirine hydrochloride). (3)

4 CONTRAINDICATIONS

- Previous hypersensitivity reaction to dolutegravir or rilpivirine. (4)
- Coadministration with dofetilide. (4)
- Coadministration with drugs where significant decreases in rilpivirine plasma concentrations may occur, which may result in loss of virologic response. (4)

5 WARNINGS AND PRECAUTIONS

- Severe skin and hypersensitivity reactions characterized by rash, constitutional findings, and sometimes organ dysfunction, including liver injury, have been reported with the individual components. Discontinue JULUCA immediately if signs or symptoms of severe skin or hypersensitivity reactions develop, as a delay in stopping treatment may result in a life-threatening reaction. (5.1)
- Hepatotoxicity has been reported in patients receiving a dolutegravir- or rilpivirine-containing regimen. Monitoring for hepatotoxicity is recommended. (5.2)
- Depressive disorders have been reported with the use of rilpivirine- or dolutegravir-containing regimens. Immediate medical evaluation is recommended for severe depressive symptoms. (5.3, 6.1)

6 ADVERSE REACTIONS

The most common adverse reactions (all grades) observed in at least 2% of subjects were diarrhea, headache, and nausea. (6.1)

To report SUSPECTED ADVERSE REACTIONS, contact ViiV Healthcare at 1-877-844-8872 or FDA at 1-800-FDA-1088 or www.fda.gov/medwatch.

7 DRUG INTERACTIONS

- Because JULUCA is a complete regimen, coadministration with other antiretroviral medications for the treatment of HIV-1 infection is not recommended. (7.1)
- Refer to the full prescribing information for important drug interactions with JULUCA. (4, 5.4, 7)
- Drugs that induce or inhibit cytochrome P450 (CYP)3A4 or uridine diphosphate glucuronosyltransferase (UGT)1A1 may affect the plasma concentrations of the components of JULUCA. (7.3)
- Drugs that increase gastric pH or containing polyvalent cations may decrease plasma concentrations of the components of JULUCA. (4, 7.3, 7.4)
- Consider alternatives to prescribing JULUCA with drugs with a known risk of Torsade de Pointes. (7.3)

8 USE IN SPECIFIC POPULATIONS

- Rilpivirine exposure during pregnancy: Total rilpivirine exposures were generally lower during pregnancy compared with the postpartum period. (8.1, 12.3).

FULL PRESCRIBING INFORMATION

1 INDICATIONS AND USAGE

JULUCA is indicated as a complete regimen for the treatment of human immunodeficiency virus type 1 (HIV-1) infection in adults to replace the current antiretroviral regimen in those who are virologically suppressed (HIV-1 RNA less than 50 copies/mL) on a stable antiretroviral regimen for at least 6 months with no history of treatment failure and no known substitutions associated with resistance to the individual components of JULUCA.

2 DOSAGE AND ADMINISTRATION

2.1 Recommended Dosage

The recommended dosage of JULUCA is one tablet taken orally once daily with a meal [see Clinical Pharmacology (12.3)]. One tablet of JULUCA contains 50 mg of dolutegravir and 25 mg of rilpivirine.

2.2 Recommended Dosage with Rifabutin Coadministration

If JULUCA is coadministered with rifabutin, take an additional 25-mg tablet of rilpivirine with JULUCA once daily with a meal for the duration of the rifabutin coadministration [see Drug Interactions (7.4)].

3 DOSAGE FORMS AND STRENGTHS

JULUCA tablets are pink, oval, biconvex tablets debossed with “SV J3T” on one side. Each film-coated tablet contains 50 mg of dolutegravir (equivalent to 52.6 mg dolutegravir sodium) and 25 mg of rilpivirine (equivalent to 27.5 mg rilpivirine hydrochloride).

4 CONTRAINDICATIONS

JULUCA is contraindicated in patients:

- with previous hypersensitivity reaction to dolutegravir or rilpivirine [see Warnings and Precautions (5.1)].
- receiving dofetilide due to the potential for increased dofetilide plasma concentrations and the risk for serious and/or life-threatening events [see Drug Interactions (7)].
- receiving other coadministered drugs in Table 1 that significantly decrease rilpivirine plasma concentrations [see Drug Interactions (7), Clinical Pharmacology (12.3)].

Table 1. Drugs That Are Contraindicated with JULUCA
Drug Class | Contraindicated Drugs in Class | Clinical Comment
Antiarrhythmic | Dofetilide | Potential for serious and/or life-threatening events due to the potential for increased dofetilide plasma concentrations.
Anticonvulsants | Carbamazepine; Oxcarbazepine; Phenobarbital; Phenytoin | Potential for significant decreases in rilpivirine plasma concentrations due to cytochrome P450 (CYP)3A enzyme induction, which may result in loss of virologic response.
Antimycobacterials | Rifampin; Rifapentine | Potential for significant decreases in rilpivirine plasma concentrations due to cytochrome P450 (CYP)3A enzyme induction, which may result in loss of virologic response.
Glucocorticoid (systemic) | Dexamethasone; (more than a single-dose treatment) | Potential for significant decreases in rilpivirine plasma concentrations due to cytochrome P450 (CYP)3A enzyme induction, which may result in loss of virologic response.
Herbal Products | St John’s wort; (Hypericum perforatum) | Potential for significant decreases in rilpivirine plasma concentrations due to cytochrome P450 (CYP)3A enzyme induction, which may result in loss of virologic response.
Proton Pump Inhibitors | e.g., Esomeprazole; Lansoprazole; Omeprazole; Pantoprazole; Rabeprazole | Potential for significant decreases in rilpivirine plasma concentrations due to gastric pH increase, which may result in loss of virologic response.

5 WARNINGS AND PRECAUTIONS

5.1 Skin and Hypersensitivity Reactions

Hypersensitivity reactions have been reported with dolutegravir and were characterized by rash, constitutional findings, and sometimes organ dysfunction, including liver injury. These events were reported in less than 1% of subjects receiving dolutegravir in Phase 3 clinical trials.

Severe skin and hypersensitivity reactions have been reported during postmarketing experience, including cases of Drug Reaction with Eosinophilia and Systemic Symptoms (DRESS), with rilpivirine-containing regimens. While some skin reactions were accompanied by constitutional symptoms such as fever, other skin reactions were associated with organ dysfunctions, including elevations in hepatic serum biochemistries. During the Phase 3 clinical trials of rilpivirine, treatment-related rashes with at least Grade 2 severity were reported in 3% of subjects. No Grade 4 rash was reported [see Adverse Reactions (6.2)].

Discontinue JULUCA immediately if signs or symptoms of severe skin or hypersensitivity reactions develop (including, but not limited to, severe rash or rash accompanied by fever, general malaise, fatigue, muscle or joint aches, blisters or peeling of the skin, mucosal involvement [oral blisters or lesions], conjunctivitis, facial edema, hepatitis, eosinophilia, angioedema, difficulty breathing). Clinical status, including laboratory parameters with liver aminotransferases, should be monitored and appropriate therapy initiated. Delay in stopping treatment with JULUCA after the onset of hypersensitivity may result in a life-threatening reaction [see Contraindications (4)].

5.2 Hepatotoxicity

Hepatic adverse events have been reported in patients receiving a dolutegravir- or rilpivirine-containing regimen [see Adverse Reactions (6.1)]. Patients with underlying hepatitis B or C or marked elevations in transaminases prior to treatment may be at increased risk for worsening or development of transaminase elevations. Additionally, in some patients receiving dolutegravir-containing regimens, the elevations in transaminases were consistent with immune reconstitution syndrome or hepatitis B reactivation particularly in the setting where anti-hepatitis therapy was withdrawn. Cases of hepatic toxicity, including elevated serum liver biochemistries and hepatitis, have also been reported in patients receiving a dolutegravir- or rilpivirine-containing regimen who had no pre-existing hepatic disease or other identifiable risk factors. Drug-induced liver injury leading to acute liver failure has been reported with dolutegravir-containing products, including liver transplant with TRIUMEQ (abacavir, dolutegravir, and lamivudine). Monitoring for hepatotoxicity is recommended.

5.3 Depressive Disorders

Depressive disorders (including depressed mood, depression, dysphoria, major depression, mood altered, negative thoughts, suicide attempt, and suicidal ideation) have been reported with rilpivirine [see Adverse Reactions (6.1)]. For information regarding depressive disorders reported in patients taking dolutegravir, [see Adverse Reactions (6.1)]. Promptly evaluate patients with severe depressive symptoms to assess whether the symptoms are related to JULUCA and to determine whether the risks of continued therapy outweigh the benefits.

5.4 Risk of Adverse Reactions or Loss of Virologic Response Due to Drug Interactions

The concomitant use of JULUCA and other drugs may result in known or potentially significant drug interactions, some of which may lead to [see Contraindications (4), Drug Interactions (7.4)]:

- Loss of therapeutic effect of JULUCA and possible development of resistance.
- Possible clinically significant adverse reactions from greater exposures of concomitant drugs.

In healthy subjects, 75 mg once daily of rilpivirine (3 times the dose in JULUCA) and 300 mg once daily (12 times the dose in JULUCA) have been shown to prolong the QTc interval of the electrocardiogram [see Drug Interactions (7.3), Clinical Pharmacology (12.2)]. Consider alternatives to JULUCA when coadministered with a drug with a known risk of Torsade de Pointes.

See Table 4 for steps to prevent or manage these possible and known significant drug interactions, including dosing recommendations. Consider the potential for drug interactions prior to and during therapy with JULUCA; review concomitant medications during therapy with JULUCA; and monitor for the adverse reactions associated with the concomitant drugs.

6 ADVERSE REACTIONS

The following adverse reactions are described below and in other sections of the labeling:

- Skin and hypersensitivity reactions [see Warnings and Precautions (5.1)].
- Hepatotoxicity [see Warnings and Precautions (5.2)].
- Depressive disorders [see Warnings and Precautions (5.3)].

6.1 Clinical Trials Experience

Because clinical trials are conducted under widely varying conditions, adverse reaction rates observed in the clinical trials of a drug cannot be directly compared with rates in the clinical trials of another drug and may not reflect the rates observed in practice.

The safety assessment of JULUCA is based on the pooled primary Week 48 analyses of data from 2 identical, international, multicenter, open-label trials, SWORD-1 and SWORD-2, including additional follow up through Week 148.

A total of 1,024 adult HIV-1-infected subjects who were on a stable suppressive antiretroviral regimen (containing 2 nucleoside reverse transcriptase inhibitors [NRTIs] plus either an integrase strand transfer inhibitor [INSTI], a non-nucleoside reverse transcriptase inhibitor [NNRTI], or a protease inhibitor [PI]) for at least 6 months with no history of treatment failure and no known substitutions associated with resistance to dolutegravir or rilpivirine, were randomized and received treatment. Subjects were randomized 1:1 to continue their current antiretroviral regimen or be switched to dolutegravir plus rilpivirine administered once daily. Subjects originally assigned to continue their current antiretroviral regimen and who remained virologically suppressed at Week 48 switched to dolutegravir plus rilpivirine at Week 52. In the pooled analyses, the proportion of subjects who discontinued treatment due to an adverse event through Week 48 was 4% in subjects receiving dolutegravir plus rilpivirine once daily and less than 1% in subjects who remained on their current antiretroviral regimen. The most common adverse events leading to discontinuation through Week 48 were psychiatric disorders: 2% of subjects receiving dolutegravir plus rilpivirine and less than 1% on the current antiretroviral regimen. In the pooled analyses, the proportion of subjects receiving dolutegravir plus rilpivirine who discontinued treatment due to an adverse event through Week 148 was 8%.

The most common adverse reactions (ARs) (all grades) reported in at least 2% of subjects in the Week 48 pooled analyses from SWORD-1 and SWORD-2 are provided in Table 2.

Table 2. Adverse Reactions (Grades 1 to 4) Reported in at Least 2% of Virologically Suppressed Subjects with HIV-1 Infection in SWORD-1 and SWORD-2 Trials (Week 48 Pooled Analyses)
Adverse Reaction | Dolutegravir plus Rilpivirine; (n = 513) | Current Antiretroviral Regimen; (n = 511)
Diarrhea | 2% | <1%
Headache | 2% | 0

In the Week 148 pooled analyses, the only adverse reaction (all grades) occurring in at least 2% of subjects who received dolutegravir plus rilpivirine and that was not observed during the Week 48 analyses was nausea (2%).

Less Common Adverse Reactions

The following ARs occurred in less than 2% of subjects receiving dolutegravir plus rilpivirine or are from studies described in the prescribing information of the individual components, TIVICAY (dolutegravir) and EDURANT (rilpivirine). Some events have been included because of their seriousness and assessment of potential causal relationship.

General Disorders: Fatigue.

Gastrointestinal Disorders: Abdominal pain, abdominal discomfort, flatulence, nausea, upper abdominal pain, vomiting.

Hepatobiliary Disorders: Cholecystitis, cholelithiasis, hepatitis.

Immune System Disorders: Immune reconstitution syndrome.

Metabolism and Nutrition Disorders: Decreased appetite.

Musculoskeletal Disorders: Myositis.

Nervous System Disorders: Dizziness, somnolence.

Psychiatric Disorders: Depressive disorders including depressed mood; depression; suicidal ideation, attempt, behavior, or completion. These events were observed primarily in subjects with a pre-existing history of depression or other psychiatric illness. Other reported psychiatric adverse reactions include anxiety, insomnia, sleep disorders, and abnormal dreams.

Renal and Urinary Disorders: Glomerulonephritis membranous, glomerulonephritis mesangioproliferative, nephrolithiasis, renal impairment.

Skin and Subcutaneous Tissue Disorders: Pruritus, rash.

Laboratory Abnormalities

Selected laboratory abnormalities with a worsening grade from baseline and representing the worst-grade toxicity in at least 2% of subjects in the Week 48 pooled analysis are presented in Table 3.

Table 3. Selected Laboratory Abnormalities (Grades 2 and 3 to 4; Week 48 Pooled Analyses) in SWORD-1 and SWORD-2 Trials
Laboratory Parameter; Preferred Term | Dolutegravir plus Rilpivirine; (n = 513) | Current Antiretroviral Regimen; (n = 511)
ALT
Grade 2 (>2.5-5.0 x ULN) | 2% | <1%
Grade 3 to 4 (>5.0 x ULN) | <1% | <1%
AST
Grade 2 (>2.5-5.0 x ULN) | <1% | 2%
Grade 3 to 4 (>5.0 x ULN) | <1% | <1%
Total Bilirubin
Grade 2 (1.6-2.5 x ULN) | 2% | 4%
Grade 3 to 4 (>2.5 x ULN) | 0 | 3%
Creatine kinase
Grade 2 (6.0-9.9 x ULN) | <1% | <1%
Grade 3 to 4 (≥10.0 x ULN) | 1% | 2%
Hyperglycemia
Grade 2 (126-250 mg/dL) | 4% | 5%
Grade 3 to 4 (>250 mg/dL) | <1% | <1%
Lipase
Grade 2 (>1.5-3.0 x ULN) | 5% | 5%
Grade 3 to 4 (>3.0 x ULN) | 2% | 2%
ALT = Alanine aminotransferase; AST = Aspartate aminotransferase; ULN = Upper limit of normal.

In the Week 148 pooled analyses, there were no additional selected laboratory abnormalities with dolutegravir plus rilpivirine compared with those shown in Table 3.

Changes in Serum Creatinine: Dolutegravir and rilpivirine have been shown to increase serum creatinine due to inhibition of tubular secretion of creatinine without affecting renal glomerular function [see Clinical Pharmacology (12.2)]. Increases in serum creatinine occurred within the first 4 weeks of treatment with dolutegravir plus rilpivirine and remained stable through 148 weeks. Mean changes from baseline of 0.093 mg/dL (range: -0.30 to 0.58 mg/dL) and 0.112 mg/dL (range: -0.24 to 0.81 mg/dL) were observed after 48 and 148 weeks of treatment with dolutegravir plus rilpivirine, respectively. These changes are not considered to be clinically relevant.

Serum Lipids: At 48 weeks, total cholesterol, HDL cholesterol, LDL cholesterol, triglycerides, and total cholesterol to HDL ratio were similar between the treatment arms, with no further notable changes beyond Week 48.

Bone Mineral Density Effects

Mean bone mineral density (BMD) increased from baseline to Week 48 in subjects who switched from an antiretroviral treatment (ART) regimen containing tenofovir disoproxil fumarate (TDF) to dolutegravir plus rilpivirine (1.34% total hip and 1.46% lumbar spine) compared with those who continued on treatment with a TDF-containing antiretroviral regimen (0.05% total hip and 0.15% lumbar spine) in a dual-energy X-ray absorptiometry (DXA) substudy. BMD declines of 5% or greater at the lumbar spine were experienced by 2% of subjects receiving JULUCA and 5% of subjects who continued their TDF-containing regimen. In subjects who received dolutegravir plus rilpivirine from study start and were continuing JULUCA at Week 148, mean BMD increases from baseline were 0.98% (total hip) and 0.53% (lumbar spine). The long-term clinical significance of these BMD changes is not known.

Fractures (excluding fingers and toes) were reported in 3 (0.6%) subjects who switched to dolutegravir plus rilpivirine and 9 (1.8%) subjects who continued their current antiretroviral regimen through 48 weeks.

Adrenal Function

In the pooled Phase 3 trials results analysis of rilpivirine, at Week 96, there was an overall mean change from baseline in basal cortisol of -0.69 (-1.12, 0.27) micrograms/dL in the rilpivirine group and of -0.02 (-0.48, 0.44) micrograms/dL in the efavirenz group. The clinical significance of the higher abnormal rate of 250 micrograms ACTH stimulation tests in the rilpivirine group is not known. Refer to the EDURANT (rilpivirine) Prescribing Information for additional information.

6.2 Postmarketing Experience

The following adverse reactions have been identified during postmarketing experience in patients receiving a dolutegravir- or rilpivirine-containing regimen. Because these reactions are reported voluntarily from a population of uncertain size, it is not always possible to reliably estimate their frequency or establish a causal relationship to drug exposure.

Blood and Lymphatic Systems

Sideroblastic anemia.

Hepatobiliary Disorders

Acute liver failure, hepatotoxicity.

Investigations

Weight increased.

Musculoskeletal Disorders

Arthralgia, myalgia.

Renal and Genitourinary Disorders

Nephrotic syndrome.

Skin and Subcutaneous Tissue Disorders

Severe skin and hypersensitivity reactions, including DRESS.

7 DRUG INTERACTIONS

7.1 Concomitant Use with Other Antiretroviral Medicines

Because JULUCA is a complete regimen, coadministration with other antiretroviral medications for the treatment of HIV-1 infection is not recommended [see Indications and Usage (1)]. Information regarding potential drug-drug interactions with other antiretroviral medications is not provided [see Contraindications (4), Warnings and Precautions (5.4), Clinical Pharmacology (12.3)].

7.2 Potential for JULUCA to Affect Other Drugs

Dolutegravir, a component of JULUCA, inhibits the renal organic cation transporters (OCT)2 and multidrug and toxin extrusion transporter (MATE)1, thus it may increase plasma concentrations of drugs eliminated via OCT2 or MATE1 such as dofetilide, dalfampridine, and metformin [see Contraindications (4), Drug Interactions (7.4)].

7.3 Potential for Other Drugs to Affect the Components of JULUCA

Dolutegravir

Dolutegravir is metabolized by uridine diphosphate (UDP)-glucuronosyl transferase (UGT)1A1 with some contribution from cytochrome P450 (CYP)3A. Dolutegravir is also a substrate of UGT1A3, UGT1A9, breast cancer resistance protein (BCRP), and P-glycoprotein (P-gp) in vitro. Drugs that induce those enzymes and transporters may decrease dolutegravir plasma concentrations and reduce the therapeutic effect of dolutegravir [see Drug Interactions (7.4)]. Coadministration of dolutegravir and other drugs that inhibit these enzymes may increase dolutegravir plasma concentrations.

Coadministration of dolutegravir with polyvalent cation-containing products may lead to decreased absorption of dolutegravir [see Drug Interactions (7.4)].

Rilpivirine

Rilpivirine is primarily metabolized by CYP3A, and drugs that induce or inhibit CYP3A may affect the clearance of rilpivirine. Coadministration of JULUCA and drugs that induce CYP3A may result in decreased plasma concentrations of rilpivirine and loss of virologic response and possible resistance to rilpivirine or to the class of NNRTIs [see Contraindications (4), Drug Interactions (7.4)]. Coadministration of JULUCA and drugs that inhibit CYP3A may result in increased plasma concentrations of rilpivirine. Coadministration of JULUCA with drugs that increase gastric pH may result in decreased plasma concentrations of rilpivirine and loss of virologic response and possible resistance to rilpivirine or to the class of NNRTIs [see Contraindications (4), Drug Interactions (7.4), Clinical Pharmacology (12.3)].

QT-Prolonging Drugs: In healthy subjects, 75 mg once daily of rilpivirine (3 times the dose in JULUCA) and 300 mg once daily (12 times the dose in JULUCA) have been shown to prolong the QTc interval of the electrocardiogram [see Clinical Pharmacology (12.2)]. Consider alternatives to JULUCA when coadministered with a drug with a known risk of Torsade de Pointes.

7.4 Established and Other Potentially Significant Drug Interactions

Information regarding potential drug interactions with dolutegravir and rilpivirine are provided in Table 4. These recommendations are based on either drug interaction trials of individual components or predicted interactions due to the expected magnitude of interaction and potential for serious adverse events or loss of efficacy [see Contraindications (4), Warnings and Precautions (5.4), Clinical Pharmacology (12.3)].

Table 4. Established and Other Potentially Significant Drug Interactions: Alterations in Dose or Regimen May Be Recommended Based on Drug Interaction Trials or Predicted Interactionsa
Concomitant Drug Class:; Drug Name | Effect on Concentration | Clinical Comment
Antacids (e.g., aluminum or magnesium hydroxide, calcium carbonate) | ↓Rilpivirine | Administer JULUCA 4 hours before or 6 hours after taking antacids.
Antiarrhythmic:; Dofetilide | ↑Dofetilide | Coadministration is contraindicated with JULUCA [see Contraindications (4)].
Anticonvulsants:; Carbamazepine; Oxcarbazepine; Phenobarbital; Phenytoin | ↓Dolutegravir; ↓Rilpivirine | Coadministration is contraindicated with JULUCA due to decreased rilpivirine concentrations [see Contraindications (4)].
Antidiabetic:; Metforminb | ↑Metformin | Refer to the prescribing information for metformin for assessing the benefit and risk of concomitant use of JULUCA and metformin.
Antimycobacterials:; Rifampin; Rifapentine | ↓Dolutegravir; ↓Rilpivirine | Coadministration is contraindicated with JULUCA due to decreased rilpivirine concentrations [see Contraindications (4)].
Antimycobacterial:; Rifabutinb | ↔Dolutegravir; ↔Rifabutin; ↓Rilpivirine | An additional rilpivirine 25-mg tablet should be taken with JULUCA once daily with a meal when rifabutin is coadministered.
Glucocorticoid (systemic):; Dexamethasone; (more than a single-dose treatment) | ↓Rilpivirine | Coadministration is contraindicated with JULUCA due to decreased rilpivirine concentrations [see Contraindications (4)].
H2-receptor antagonists:; Famotidine; Cimetidine; Nizatidine; Ranitidine | ↔Dolutegravir; ↓Rilpivirine | JULUCA should only be administered at least 4 hours before or 12 hours after taking H2-receptor antagonists.
Herbal product:; St John’s wort (Hypericum perforatum) | ↓Dolutegravir; ↓Rilpivirine | Coadministration is contraindicated with JULUCA due to decreased rilpivirine concentrations [see Contraindications (4)].
Macrolide or ketolide antibiotics:; Clarithromycin; Erythromycin; Telithromycin | ↔Dolutegravir; ↑Rilpivirine | Where possible, consider alternatives, such as azithromycin.
Medications containing polyvalent cations (e.g., Mg or Al):; Cation-containing productsb or laxatives; Sucralfate; Buffered medications | ↓Dolutegravir | Administer JULUCA 4 hours before or 6 hours after taking products containing polyvalent cations.
Narcotic analgesic:; Methadoneb | ↔Dolutegravir; ↓Methadone; ↔Rilpivirine | No dose adjustments are required when starting coadministration of methadone with JULUCA. However, clinical monitoring is recommended as methadone maintenance therapy may need to be adjusted in some patients.
Oral calcium and iron supplements, including multivitamins containing calcium or ironb (non-antacid) | ↓Dolutegravir | Administer JULUCA and supplements containing calcium or iron together with a meal or take JULUCA 4 hours before or 6 hours after taking these supplements.
Potassium channel blocker:; Dalfampridine | ↑Dalfampridine | Elevated levels of dalfampridine increase the risk of seizures. The potential benefits of taking dalfampridine concurrently with JULUCA should be considered against the risk of seizures in these patients.
Proton pump inhibitors:; e.g., Esomeprazole; Lansoprazole; Omeprazole; Pantoprazole; Rabeprazole | ↓Rilpivirine | Coadministration is contraindicated with JULUCA due to decreased rilpivirine concentrations [see Contraindications (4)].
↑ = Increase, ↓ = Decrease, ↔ = No change.
a This table is not all inclusive.
b See Clinical Pharmacology (12.3) for magnitude of interaction.

8 USE IN SPECIFIC POPULATIONS

8.1 Pregnancy

Pregnancy Exposure Registry

There is a pregnancy exposure registry that monitors pregnancy outcomes in individuals exposed to JULUCA during pregnancy. Healthcare providers are encouraged to register patients by calling the Antiretroviral Pregnancy Registry (APR) at 1-800-258-4263.

Risk Summary

Data from two, ongoing birth outcome surveillance studies in Botswana and Eswatini which together include over 14,000 individuals evaluated during pregnancy show similar prevalence of neural tube defects among infants born to individuals taking dolutegravir at the time of conception compared to those born to individuals taking non-dolutegravir-containing regimens at conception or infants born to HIV-negative individuals (see Data).

There are insufficient human data on the use of JULUCA during pregnancy to definitively assess a drug-associated risk for birth defects and miscarriage. However, available human data from the APR with the individual components of JULUCA do not indicate an increased risk of birth defects (see Data). The background risk for major birth defects for the indicated population is unknown. In the U.S. general population, the estimated background rate for major birth defects and miscarriage in clinically recognized pregnancies is 2% to 4% and 15% to 20%, respectively.

In animal reproduction studies, no evidence of adverse developmental outcomes (including neural tube defects) was observed with the components of JULUCA at systemic exposures (AUC) to dolutegravir less than (rabbits) and 38 times (rats) and exposures to rilpivirine 15 (rats) and 70 (rabbits) times the exposure at the recommended human dose (RHD) of JULUCA (see Data).

Data

Human Data:

Dolutegravir:

Observational studies: The first interim analysis from an ongoing birth outcome surveillance study in Botswana identified an association between dolutegravir and an increased risk of neural tube defects when dolutegravir was administered at the time of conception and in early pregnancy. A subsequent analysis was conducted based on a larger cohort from the birth outcome surveillance study in Botswana and included over 9,460 individuals exposed to dolutegravir at conception, 23,664 individuals exposed to non-dolutegravir-containing regimens, and 170,723 HIV-negative pregnant individuals. The prevalence of neural tube defects in infants delivered to individuals taking dolutegravir at conception was 0.11% (95% CI: 0.05-0.19%). The observed prevalence rate did not differ significantly from that of infants delivered to individuals taking non-dolutegravir-containing regimens (0.11%, 95% CI: 0.07-0.16%), or to HIV-negative individuals (0.06%, 95% CI: 0.05-0.08%).

The Eswatini birth outcome surveillance study includes 9,743 individuals exposed to dolutegravir at conception, 1,838 individuals exposed to non-dolutegravir-containing regimens, and 32,259 HIV-negative pregnant individuals. The prevalence of neural tube defects in infants delivered to individuals taking dolutegravir at conception was 0.08% (95% CI: 0.04-0.16%). The observed prevalence rate did not differ significantly from that of infants delivered to individuals taking non-dolutegravir-containing regimens (0.22%, 95% CI: 0.06-0.56%) or to HIV-negative individuals (0.08%, 95% CI: 0.06-0.12%). The observed prevalence of neural tube defects in infants delivered to individuals taking non-dolutegravir-containing regimens had a wide confidence interval due to low sample size.

Limitations of these birth outcome surveillance studies include insufficient data to determine if baseline characteristics were balanced between the study groups or to assess other factors such as the use of folic acid during the preconception or first trimester periods.

Antiretroviral Pregnancy Registry: Based on prospective reports to the APR, of 1,377 exposures to dolutegravir during pregnancy resulting in live births (including 874 exposed in the first trimester), the prevalence of defects in live births was 3.3% (95% CI: 2.2% to 4.7%) following first-trimester exposure to dolutegravir-containing regimens and 5.0% (95% CI: 3.2% to 7.3%) following second-/third-trimester exposure to dolutegravir-containing regimens. In the U.S. reference population of the Metropolitan Atlanta Congenital Defects Program (MACDP), the background birth defect rate was 2.7%.

Dolutegravir has been shown to cross the placenta. In a clinical trial in Uganda and South Africa in women during the last trimester of pregnancy receiving dolutegravir 50 mg once daily, the ratio of median dolutegravir concentration in fetal umbilical cord to that in maternal peripheral plasma was 1.21 (range 0.51 to 2.11) (n = 15).

Rilpivirine: Based on prospective reports to the APR of over 870 exposures to rilpivirine-containing regimens during pregnancy resulting in live births (including over 660 exposed during the first trimester and over 210 exposed in the second/third trimester), there was no significant difference between the overall risk of birth defects for rilpivirine compared with the background birth defect rate of 2.7% in the U.S. reference population of the MACDP. The prevalence of defects in live births was 2.1% (95% CI: 1.1% to 3.5%) and 0.9% (95% CI: 0.1% to 3.4%) following first and second/third trimester exposure, respectively, to rilpivirine-containing regimens.

Rilpivirine in combination with a background regimen was evaluated in a clinical trial of 19 HIV-1–infected pregnant subjects during the second and third trimesters and postpartum. Each of the subjects were on a rilpivirine-based regimen at the time of enrollment. Twelve subjects completed the trial through the postpartum period (6 to 12 weeks after delivery) and pregnancy outcomes are missing for 6 subjects. The exposure (C0h and AUC) of total rilpivirine was approximately 30% to 40% lower during pregnancy compared with postpartum (6 to 12 weeks). The protein binding of rilpivirine was similar (>99%) during the second trimester, third trimester, and the postpartum period [see Clinical Pharmacology (12.3)]. One subject discontinued the trial following fetal death at 25 weeks’ gestation due to suspected premature rupture of membranes. Among the 12 subjects who were virologically suppressed at baseline (less than 50 copies/mL), virologic response was preserved in 10 subjects (83.3%) through the third trimester visit and in 9 subjects (75%) through the 6- to 12-week postpartum visit. Virologic outcomes during the third trimester visit were missing for 2 subjects who were withdrawn (one subject was nonadherent to the study drug and one subject withdrew consent). Among the 10 infants with HIV test results available, born to 10 HIV-1–infected pregnant subjects, all had negative test results for HIV-1 at the time of delivery and up to 16 weeks postpartum. All 10 infants received antiretroviral prophylactic treatment with zidovudine. Rilpivirine was well tolerated during pregnancy and postpartum. There were no new safety findings compared with the known safety profile of rilpivirine in HIV-1–infected adults.

Animal Data:

Dolutegravir: Dolutegravir was administered orally at up to 1,000 mg/kg daily to pregnant rats and rabbits on Gestation Days 6 to 17 and 6 to 18, respectively, and to rats on Gestation Day 6 to Lactation/Post-partum Day 20. No adverse effects on embryo-fetal (rats and rabbits) development were observed at up to the highest dose tested. During organogenesis, systemic exposures (AUC) to dolutegravir in rabbits were less than the exposure in humans, and in rats were approximately 38 times the exposure in humans (50 mg once daily). In the rat pre/post-natal development study, decreased body weight of the developing offspring was observed during lactation at a maternally toxic dose (approximately 32 times the human exposure with 50 mg once daily).

Rilpivirine: Rilpivirine was administered orally to pregnant rats (40, 120, or 400 mg/kg/d) and rabbits (5, 10, or 20 mg/kg/day) through organogenesis (on Gestation Days 6 through 17, and 6 through 19, respectively). No significant toxicological effects were observed in embryo-fetal toxicity studies performed with rilpivirine in rats and rabbits at exposures 15 (rats) and 70 (rabbits) times higher than the exposure in humans at the recommended dose of 25 mg once daily. In a pre/postnatal development study with rilpivirine, where rats were administered up to 400 mg/kg/day through lactation, no significant adverse effects directly related to drug were noted in the offspring.

8.2 Lactation

Risk Summary

Dolutegravir is present in human milk. It is not known whether dolutegravir affects human milk production or have effects on the breastfed infant. When administered to lactating rats, rilpivirine was present in milk (see Data).

Potential risks of breastfeeding include: (1) HIV‑1 transmission (in HIV-1–negative infants), (2) developing viral resistance (in HIV-1–positive infants), and (3) adverse reactions in a breastfed infant similar to those seen in adults.

Data

Animal Data: Rilpivirine: In animals, no studies have been conducted to assess the excretion of rilpivirine into milk directly; however, rilpivirine was present in plasma of rat pups exposed through the milk of lactating rats (dosed up to 400 mg/kg/day).

8.4 Pediatric Use

The safety and efficacy of JULUCA have not been established in pediatric patients.

8.5 Geriatric Use

Clinical trials of JULUCA did not include sufficient numbers of subjects aged 65 and older to determine whether they respond differently from younger subjects. In general, caution should be exercised in administration of JULUCA in elderly patients reflecting greater frequency of decreased hepatic, renal, or cardiac function, and of concomitant disease or other drug therapy [see Clinical Pharmacology (12.3)].

8.6 Renal Impairment

No dosage adjustment is necessary for patients with mild or moderate renal impairment (creatinine clearance greater than or equal to 30 mL/min) [see Clinical Pharmacology (12.3)]. In patients with severe renal impairment (creatinine clearance less than 30 mL/min) or end-stage renal disease, increased monitoring for adverse effects is recommended.

8.7 Hepatic Impairment

No dosage adjustment is necessary for patients with mild to moderate hepatic impairment (Child-Pugh Score A or B). The effect of severe hepatic impairment (Child-Pugh Score C) on the pharmacokinetics of dolutegravir or rilpivirine is unknown [see Clinical Pharmacology (12.3)].

10 OVERDOSAGE

There is no known specific treatment for overdose with JULUCA. If overdose occurs, the patient should be monitored and standard supportive treatment applied as required, including monitoring of vital signs and ECG (QT interval) as well as observation of the clinical status of the patient. As both dolutegravir and rilpivirine are highly bound to plasma proteins, it is unlikely that either would be significantly removed by dialysis.

11 DESCRIPTION

JULUCA is a fixed-dose combination tablet containing dolutegravir (as dolutegravir sodium), an INSTI, and rilpivirine (as rilpivirine hydrochloride), an NNRTI.

The chemical name of dolutegravir sodium is sodium (4R,12aS)-9-{[(2,4-difluorophenyl)methyl]carbamoyl}-4-methyl-6,8-dioxo-3,4,6,8,12,12a-hexahydro-2H-pyrido[1',2':4,5]pyrazino[2,1-b][1,3]oxazin-7-olate. The empirical formula is C20H18F2N3NaO5, and the molecular weight is 441.36 g/mol. It has the following structural formula:

Dolutegravir sodium is a white to light yellow powder and is slightly soluble in water.

The chemical name for rilpivirine hydrochloride is 4-[[4-[[4-[(E)-2-cyanoethenyl]-2,6-dimethylphenyl]amino]-2-pyrimidinyl]amino]benzonitrile monohydrochloride. Its molecular formula is C22H18N6 • HCl and its molecular weight is 402.88 g/mol. Rilpivirine hydrochloride has the following structural formula:

Rilpivirine hydrochloride is a white to almost white powder. Rilpivirine hydrochloride is practically insoluble in water over a wide pH range.

JULUCA tablets are for oral administration. Each film-coated tablet contains the active ingredients 50 mg of dolutegravir (equivalent to 52.6 mg dolutegravir sodium) and 25 mg of rilpivirine (equivalent to 27.5 mg rilpivirine hydrochloride) and the inactive ingredients croscarmellose sodium, D-mannitol, lactose monohydrate, magnesium stearate, microcrystalline cellulose, polysorbate 20, povidone K29/32 and K30, silicified microcrystalline cellulose, sodium starch glycolate, and sodium stearyl fumarate. The tablet film‑coating contains the inactive ingredients iron oxide red, iron oxide yellow, macrogol/PEG, polyvinyl alcohol-part hydrolyzed, talc, and titanium dioxide.

12 CLINICAL PHARMACOLOGY

12.1 Mechanism of Action

JULUCA is a fixed-dose combination of the HIV-1 antiretroviral agents, dolutegravir and rilpivirine [see Microbiology (12.4)].

12.2 Pharmacodynamics

Cardiac Electrophysiology

The effect of JULUCA on the QT interval has not been studied.

In a randomized, placebo-controlled, crossover trial, 42 healthy subjects received single-dose oral administration of placebo, dolutegravir 250-mg suspension (exposures approximately 3‑fold of the 50-mg once-daily dose at steady state), and moxifloxacin 400 mg (active control) in random sequence. After baseline and placebo adjustment, the maximum mean QTc change based on Fridericia correction method (QTcF) for dolutegravir was 2.4 msec (1-sided 95% upper CI: 4.9 msec). Dolutegravir did not prolong the QTc interval over 24 hours postdose.

The effect of rilpivirine at the recommended dose of 25 mg once daily on the QTcF interval was evaluated in a randomized, placebo- and active- (moxifloxacin 400 mg once daily) controlled crossover study in 60 healthy adults, with 13 measurements over 24 hours at steady state. The maximum mean time-matched (95% upper confidence bound) differences in QTcF interval from placebo after baseline correction was 2.0 (5.0) milliseconds (i.e., below the threshold of clinical concern). When 75 mg and 300 mg once daily of rilpivirine (3 times and 12 times the recommended dosage in JULUCA, respectively) were studied in healthy adults, the maximum mean time-matched (95% upper confidence bound) differences in QTcF interval from placebo after baseline correction were 10.7 (15.3) and 23.3 (28.4) milliseconds, respectively. Steady-state administration of rilpivirine 75 mg once daily and 300 mg once daily resulted in a mean steady-state Cmax approximately 2.6-fold and 6.7-fold, respectively, higher than the mean Cmax observed with the recommended 25-mg once-daily dose of rilpivirine [see Drug Interactions (7.4)].

Effects on Renal Function

The effect of dolutegravir on renal function was evaluated in an open-label, randomized, 3-arm, parallel, placebo-controlled trial in healthy subjects (n = 37) who received dolutegravir 50 mg once daily (n = 12), dolutegravir 50 mg twice daily (n = 13), or placebo once daily (n = 12) for 14 days. A decrease in creatinine clearance, as determined by 24-hour urine collection, was observed with both doses of dolutegravir after 14 days of treatment in subjects who received 50 mg once daily (9% decrease) and 50 mg twice daily (13% decrease). Neither dose of dolutegravir had a significant effect on the actual glomerular filtration rate (determined by the clearance of probe drug, iohexol) or effective renal plasma flow (determined by the clearance of probe drug, para-amino hippurate) compared with the placebo.

12.3 Pharmacokinetics

Absorption, Distribution, Metabolism, and Excretion

The pharmacokinetic (PK) properties of the components of JULUCA are provided in Table 5. The multiple-dose pharmacokinetic parameters are provided in Table 6.

Table 5. Pharmacokinetic Properties of the Components of JULUCA
 | Dolutegravir | Rilpivirine
Absorption
Tmax (h) | 3 | 4
Effect of moderate-fat meal (relative to fasting)a | AUC Ratio 1.87 (1.54, 2.26) | AUC Ratio 1.57 (1.24, 1.98)
Effect of high-fat meal (relative to fasting)a | AUC Ratio 1.87 (1.53, 2.29) | AUC Ratio 1.72 (1.36, 2.16)
Distribution
% Bound to human plasma proteins | ~99 | ~99
Source of protein binding data | in vitro | in vitro
Blood-to-plasma ratio | 0.5 | 0.7
Metabolism
Primarily metabolized | UGT1A1; CYP3A (minor) | CYP3A
Elimination
Major route of elimination | Metabolism | Metabolism
t1/2 (h) | 14 | 50
% of dose excreted as total ^14C (unchanged drug) in urineb | 31 (<1) | 6.5 (<1)
% of dose excreted as total ^14C (unchanged drug) in fecesb | 64 (53) | 85 (25)
UGT = uridine diphosphate glucuronosyltransferase; CYP = Cytochrome P450.
a Geometric mean ratio (fed/fasted) in PK parameters and (90% confidence interval). High-calorie/high-fat meal = ~900 kcal, 56% fat. Moderate-fat meal = ~625 kcal, 32% fat. When rilpivirine was taken with only a protein-rich nutritional drink, exposures were 50% lower than when taken with a meal.
b Dosing in mass balance studies: single-dose administration of [^14C] dolutegravir or [^14C] rilpivirine.

Table 6. Multiple-Dose Pharmacokinetic Properties of the Components of JULUCA
Parameter Mean (CV%) | Dolutegravira | Rilpivirinea
Cmax (mcg/mL) | 3.67 (20) | 0.13 (54)b
AUCtau (mcg/h/mL) | 53.6 (27) | 2.2 (38)
Ctrough (mcg/mL) | 1.11 (46) | 0.08 (44)
a Based on population pharmacokinetic analyses using pooled data from ART treatment-naïve adults receiving 50 mg dolutegravir once daily or 25 mg rilpivirine once daily.
b Observed Cmax in a pharmacokinetic substudy in ART treatment-naïve adults receiving 25 mg rilpivirine once daily.

Specific Populations

Pediatric Patients: The pharmacokinetics of dolutegravir plus rilpivirine has not been studied in pediatric subjects [see Use in Specific Populations (8.4)].

Geriatric Patients: Population pharmacokinetic analyses from studies with the individual components indicated age had no clinically relevant effect on the pharmacokinetics of dolutegravir or rilpivirine. Pharmacokinetic data in subjects 65 years of age and older are limited [see Use in Specific Populations (8.5)].

Patients with Renal Impairment: Population pharmacokinetic analyses indicated that mild and moderate renal impairment had no clinically relevant effect on the exposure of dolutegravir. Dolutegravir AUC, Cmax, and C24 were lower by 40%, 23%, and 43%, respectively, in subjects (n = 8) with severe renal impairment (creatinine clearance less than 30 mL/min) as compared with matched healthy controls. There is inadequate information to recommend appropriate dosing of dolutegravir in patients requiring dialysis [see Use in Specific Populations (8.6)].

Population pharmacokinetic analyses indicated that mild renal impairment had no clinically relevant effect on the exposure of rilpivirine. There is limited or no information regarding the pharmacokinetics of rilpivirine in patients with moderate or severe renal impairment, end-stage renal disease, or patients requiring dialysis.

Patients with Hepatic Impairment: Dolutegravir exposures were similar in subjects (n = 8) with moderate hepatic impairment (Child-Pugh Score B) as compared with matched healthy controls. The effect of severe hepatic impairment (Child-Pugh Score C) on the pharmacokinetics of dolutegravir has not been studied.

Rilpivirine exposure was 47% higher in subjects (n = 8) with mild hepatic impairment (Child-Pugh Score A) and 5% higher in subjects (n = 8) with moderate hepatic impairment (Child-Pugh Score B) compared with matched controls. The effect of severe hepatic impairment (Child-Pugh Score C) on the pharmacokinetics of rilpivirine has not been studied [see Use in Specific Populations (8.7)].

Patients with HBV/HCV Co-infection: Population pharmacokinetic analyses indicated that hepatitis C virus co-infection had no clinically relevant effect on the exposure of dolutegravir or rilpivirine. Subjects with hepatitis B co-infection were excluded from studies with dolutegravir plus rilpivirine.

Gender and Race: Population pharmacokinetic analyses from studies with the individual components revealed that gender and race had no clinically relevant effect on the pharmacokinetics of dolutegravir or rilpivirine.

Pregnancy and Postpartum: Rilpivirine: The exposure (C0h and AUC24h) to total rilpivirine after taking rilpivirine 25 mg once daily as part of an antiretroviral regimen was 30% to 40% lower during pregnancy (similar for the second and third trimesters) compared with postpartum (see Table 7). However, the exposure during pregnancy was not significantly different from exposures obtained in Phase 3 trials of rilpivirine-containing regimens. Based on the exposure-response relationship for rilpivirine, this decrease is not considered clinically relevant in patients who are virologically suppressed. The protein binding of rilpivirine was similar (>99%) during the second trimester, third trimester, and postpartum.

Table 7. Pharmacokinetic Results of Rilpivirine during the 2nd and 3rd Trimesters of Pregnancy and Postpartum Perioda
Pharmacokinetics of; Total Rilpivirine; (mean ± SD) | Postpartum (6 to 12 Weeks); (n = 11) | 2nd Trimester of Pregnancy; (n = 15) | 3rd Trimester of Pregnancy; (n = 13)
C0h (ng/mL) | 111 ± 69.2 | 65.0 ± 23.9 | 63.5 ± 26.2
Cmin (ng/mL) | 84.0 ± 58.8 | 54.3 ± 25.8 | 52.9 ± 24.4
Cmax (ng/mL) | 167 ± 101 | 121 ± 45.9 | 123 ± 47.5
Tmax (h), median (range) | 4.00 (2.03-25.08) | 4.00 (1.00-9.00) | 4.00 (2.00-24.93)
AUC24h (ng•h/mL) | 2,714 ± 1,535 | 1,792 ± 711 | 1,762 ± 662
a Total rilpivirine exposure after administration of rilpivirine 25 mg once daily as part of an antiretroviral regimen.

Drug Interaction Studies

Drug interaction trials were conducted with dolutegravir or rilpivirine as individual components and other drugs likely to be coadministered or commonly used as probes for pharmacokinetic interactions. In vitro, dolutegravir did not inhibit (IC50 greater than 50 microM) the following: CYP1A2, CYP2A6, CYP2B6, CYP2C8, CYP2C9, CYP2C19, CYP2D6, CYP3A, UGT1A1, UGT2B7, P‑gp, BCRP, bile salt export pump (BSEP), organic anion transporter polypeptide (OATP)1B1, OATP1B3, OCT1, multidrug resistance protein (MRP)2, or MRP4. In vitro, dolutegravir did not induce CYP1A2, CYP2B6, or CYP3A4.

In vitro, dolutegravir inhibited the renal OCT2 (IC50 = 1.93 microM) and MATE1 (IC50 = 6.34 microM). In vivo, dolutegravir inhibits tubular secretion of creatinine by inhibiting OCT2 and potentially MATE1. Dolutegravir may increase plasma concentrations of drugs eliminated via OCT2 or MATE1 such as dofetilide, dalfampridine, and metformin [see Contraindications (4), Drug Interactions (7.4)].

In vitro, dolutegravir inhibited the basolateral renal transporters, organic anion transporter (OAT)1 (IC50 = 2.12 microM) and OAT3 (IC50 = 1.97 microM). However, in vivo, dolutegravir did not alter the plasma concentrations of tenofovir or para-amino hippurate, substrates of OAT1 and OAT3.

Dolutegravir is metabolized by UGT1A1 with some contribution from CYP3A. Dolutegravir is also a substrate of UGT1A3, UGT1A9, BCRP, and P-gp in vitro. In vitro, dolutegravir was not a substrate of OATP1B1 or OATP1B3.

Rilpivirine is primarily metabolized by CYP3A. Rilpivirine 25 mg once daily is not likely to have a clinically relevant effect on the exposure of medicinal products metabolized by CYP enzymes.

Dosing recommendations as a result of established and other potentially significant drug-drug interactions with dolutegravir or rilpivirine are provided in Table 4 [see Drug Interactions (7.4)].

Table 8. Summary of Effect of Dolutegravir on the Pharmacokinetics of Coadministered Drugs
Coadministered Drug(s); and Dose(s) | Dose of Dolutegravir | n | Geometric Mean Ratio (90% CI) of Pharmacokinetic Parameters of Coadministered Drug with/without Dolutegravir; No Effect = 1.00
Coadministered Drug(s); and Dose(s) | Dose of Dolutegravir | n | Cmax | AUC | Cτ or C24
Ethinyl estradiol; 0.035 mg | 50 mg; twice daily | 15 | 0.99; (0.91 to 1.08) | 1.03; (0.96 to 1.11) | 1.02; (0.93 to 1.11)
Metformin; 500 mg twice daily | 50 mg; once daily | 15a | 1.66; (1.53 to 1.81) | 1.79; (1.65 to 1.93) | _
Metformin; 500 mg twice daily | 50 mg; twice daily | 15a | 2.11; (1.91 to 2.33) | 2.45; (2.25 to 2.66) | _
Methadone; 16 to 150 mg | 50 mg; twice daily | 11 | 1.00; (0. 94 to 1.06) | 0.98; (0.91 to 1.06) | 0.99; (0.91 to 1.07)
Midazolam; 3 mg | 25 mg; once daily | 10 | _ | 0.95; (0.79 to 1.15) | _
Norelgestromin; 0.25 mg | 50 mg; twice daily | 15 | 0.89; (0.82 to 0.97) | 0.98; (0.91 to 1.04) | 0.93; (0.85 to 1.03)
a The number of subjects represents the maximum number of subjects that were evaluated.

Table 9. Summary of Effect of Coadministered Drugs on the Pharmacokinetics of Dolutegravir
Coadministered Drug(s); and Dose(s) | Dose of Dolutegravir | n | Geometric Mean Ratio (90% CI) of Dolutegravir Pharmacokinetic Parameters with/without Coadministered Drugs No Effect = 1.00
Coadministered Drug(s); and Dose(s) | Dose of Dolutegravir | n | Cmax | AUC | Cτ or C24
Antacid (MAALOX); simultaneous administration | 50 mg; single dose | 16 | 0.28; (0.23 to 0.33) | 0.26; (0.22 to 0.32) | 0.26; (0.21 to 0.31)
Antacid (MAALOX); 2 h after dolutegravir | 50 mg; single dose | 16 | 0.82; (0.69 to 0.98) | 0.74; (0.62 to 0.90) | 0.70; (0.58 to 0.85)
Calcium carbonate 1,200 mg; simultaneous administration (fasted) | 50 mg; single dose | 12 | 0.63; (0.50 to 0.81) | 0.61; (0.47 to 0.80) | 0.61; (0.47 to 0.80)
Calcium carbonate 1,200 mg; simultaneous administration (fed) | 50 mg; single dose | 11 | 1.07; (0.83 to 1.38) | 1.09; (0.84 to 1.43) | 1.08; (0.81 to 1.42)
Calcium carbonate 1,200 mg; 2 h after dolutegravir | 50 mg; single dose | 11 | 1.00; (0.78 to 1.29) | 0.94; (0.72 to 1.23) | 0.90; (0.68 to 1.19)
Carbamazepine; 300 mg twice daily | 50 mg; once daily | 16c | 0.67; (0.61 to 0.73) | 0.51; (0.48 to 0.55) | 0.27; (0.24 to 0.31)
Ferrous fumarate 324 mg; simultaneous administration (fasted) | 50 mg; single dose | 11 | 0.43; (0.35 to 0.52) | 0.46; (0.38 to 0.56) | 0.44; (0.36 to 0.54)
Ferrous fumarate 324 mg; simultaneous administration (fed) | 50 mg; single dose | 11 | 1.03; (0.84 to 1.26) | 0.98; (0.81 to 1.20) | 1.00; (0.81 to 1.23)
Ferrous fumarate 324 mg; 2 h after dolutegravir | 50 mg; single dose | 10 | 0.99; (0.81 to 1.21) | 0.95; (0.77 to 1.15) | 0.92; (0.74 to 1.13)
Multivitamin (One-A-Day); simultaneous administration | 50 mg; single dose | 16 | 0.65; (0.54 to 0.77) | 0.67; (0.55 to 0.81) | 0.68; (0.56 to 0.82)
Omeprazole; 40 mg once daily | 50 mg; single dose | 12 | 0.92; (0.75 to 1.11) | 0.97; (0.78 to 1.20) | 0.95; (0.75 to 1.21)
Prednisone; 60 mg once daily with taper | 50 mg; once daily | 12 | 1.06; (0.99 to 1.14) | 1.11; (1.03 to 1.20) | 1.17; (1.06 to 1.28)
Rifampina; 600 mg once daily | 50 mg; twice daily | 11 | 0.57; (0.49 to 0.65) | 0.46; (0.38 to 0.55) | 0.28; (0.23 to 0.34)
Rifampinb; 600 mg once daily | 50 mg; twice daily | 11 | 1.18; (1.03 to 1.37) | 1.33; (1.15 to 1.53) | 1.22; (1.01 to 1.48)
Rifabutin; 300 mg once daily | 50 mg; once daily | 9 | 1.16; (0.98 to 1.37) | 0.95; (0.82 to 1.10) | 0.70; (0.57 to 0.87)
a Comparison is rifampin taken with dolutegravir 50 mg twice daily compared with dolutegravir 50 mg twice daily.
b Comparison is rifampin taken with dolutegravir 50 mg twice daily compared with dolutegravir 50 mg once daily.
c The number of subjects represents the maximum number of subjects that were evaluated.

Table 10. Summary of Effect of Rilpivirine on the Pharmacokinetics of Coadministered Drugs
Coadministered Drug(s); and Dose(s) | Dose of Rilpivirine | n | Geometric Mean Ratio (90% CI) of Coadministered Drug Pharmacokinetic Parameters with/without EDURANT No Effect = 1.00
Coadministered Drug(s); and Dose(s) | Dose of Rilpivirine | n | Cmax | AUC | Cmin
Acetaminophen; 500 mg single dose | 150 mg; once dailya | 16 | 0.97; (0.86 to 1.10) | 0.91; (0.86 to 0.97) | NA
Atorvastatin; 40 mg once daily | 150 mg; once dailya | 16 | 1.35; (1.08 to 1.68) | 1.04; (0.97 to 1.12) | 0.85; (0.69 to 1.03)
2-hydroxy-atorvastatin |  |  | 1.58; (1.33 to 1.87) | 1.39; (1.29 to 1.50) | 1.32; (1.10 to 1.58)
4-hydroxy-atorvastatin |  |  | 1.28; (1.15 to 1.43) | 1.23; (1.13 to 1.33) | NA
Chlorzoxazone; 500 mg single dose taken 2 hours after rilpivirine | 150 mg; once dailya | 16 | 0.98; (0.85 to 1.13) | 1.03; (0.95 to 1.13) | NA
Digoxin; 0.5 mg single dose | 25 mg; once daily | 22 | 1.06; (0.97 to 1.17) | 0.98; (0.93 to 1.04)c | NA
Ethinylestradiol; 0.035 mg once daily | 25 mg; once daily | 17 | 1.17; (1.06 to 1.30) | 1.14; (1.10 to 1.19) | 1.09; (1.03 to 1.16)
Norethindrone; 1 mg once daily |  |  | 0.94; (0.83 to 1.06) | 0.89; (0.84 to 0.94) | 0.99; (0.90 to 1.08)
Ketoconazole; 400 mg once daily | 150 mg; once dailya | 14 | 0.85; (0.80 to 0.90) | 0.76; (0.70 to 0.82) | 0.34; (0.25 to 0.46)
Methadone; 60-100 mg once daily, individualized dose | 25 mg; once daily | 13
R(‑) methadone |  |  | 0.86; (0.78 to 0.95) | 0.84; (0.74 to 0.95) | 0.78; (0.67 to 0.91)
S(+) methadone |  |  | 0.87; (0.78 to 0.97) | 0.84; (0.74 to 0.96) | 0.79; (0.67 to 0.92)
Metformin; 850 mg single dose | 25 mg; once daily | 20 | 1.02; (0.95 to -1.10) | 0.97; (0.90 to 1.06)b | NA
Omeprazole; 20 mg once daily | 150 mg; once dailya | 15 | 0.86; (0.68 to 1.09) | 0.86; (0.76 to 0.97) | NA
Rifampin; 600 mg once daily | 150 mg; once dailya | 16 | 1.02; (0.93 to 1.12) | 0.99; (0.92 to 1.07) | NA
25-desacetylrifampin |  |  | 1.00; (0.87 to 1.15) | 0.91; (0.77 to 1.07) | NA
Sildenafil; 50 mg single dose | 75 mg; once dailya | 16 | 0.93; (0.80 to 1.08) | 0.97; (0.87 to 1.08) | NA
N-desmethyl-sildenafil |  |  | 0.90; (0.80 to 1.02) | 0.92; (0.85 to 0.99)c | NA
Simeprevir; 150 mg once daily | 25 mg; once daily | 21 | 1.10; (0.97 to 1.26) | 1.06; (0.94 to 1.19) | 0.96; (0.83 to 1.11)
n = Maximum number of subjects with data; NA = Not available.
a This interaction study has been performed with a dose higher than the recommended dose for rilpivirine (25 mg once daily) assessing the maximal effect on the coadministered drug.
b N (maximum number of subjects with data) for AUC(0-∞) = 15.
c AUC(0-last).

Table 11. Summary of Effect of Coadministered Drugs on the Pharmacokinetics of Rilpivirine
Coadministered Drug(s); and Dose(s) | Dose of Rilpivirine | n | Geometric Mean Ratio (90% CI) of Rilpivirine Pharmacokinetic Parameters with/without Coadministered Drugs No Effect = 1.00
Coadministered Drug(s); and Dose(s) | Dose of Rilpivirine | n | Cmax | AUC | Cmin
Acetaminophen; 500 mg single dose | 150 mg; once dailya | 16 | 1.09; (1.01 to 1.18) | 1.16; (1.10 to 1.22) | 1.26; (1.16 to 1.38)
Atorvastatin; 40 mg once daily | 150 mg; once dailya | 16 | 0.91; (0.79 to 1.06) | 0.90; (0.81 to 0.99) | 0.90; (0.84 to 0.96)
Chlorzoxazone; 500 mg single dose taken 2 hours after rilpivirine | 150 mg; once dailya | 16 | 1.17; (1.08 to 1.27) | 1.25; (1.16 to 1.35) | 1.18; (1.09 to 1.28)
Ethinylestradiol/ Norethindrone; 0.035 mg once daily/ 1 mg once daily | 25 mg; once daily | 15 | ↔b | ↔b | ↔b
Famotidine; 40 mg single dose taken 12 hours before rilpivirine | 150 mg; single dosea | 24 | 0.99; (0.84 to 1.16) | 0.91; (0.78 to 1.07) | NA
Famotidine; 40 mg single dose taken 2 hours before rilpivirine | 150 mg; single dosea | 23 | 0.15; (0.12 to 0.19) | 0.24; (0.20 to 0.28) | NA
Famotidine; 40 mg single dose taken 4 hours after rilpivirine | 150 mg; single dosea | 24 | 1.21; (1.06 to 1.39) | 1.13; (1.01 to 1.27) | NA
Ketoconazole; 400 mg once daily | 150 mg; once dailyb | 15 | 1.30; (1.13 to 1.48) | 1.49; (1.31 to 1.70) | 1.76; (1.57 to 1.97)
Methadone; 60-100 mg once daily, individualized dose | 25 mg; once daily | 12 | ↔b | ↔b | ↔b
Omeprazole; 20 mg once daily | 150 mg; once dailya | 16 | 0.60; (0.48 to 0.73) | 0.60; (0.51 to 0.71) | 0.67; (0.58 to 0.78)
Rifabutin; 300 mg once daily | 25 mg; once daily | 18 | 0.69; (0.62 to 0.76) | 0.58; (0.52 to 0.65) | 0.52; (0.46 to 0.59)
Rifabutin; 300 mg once daily | 50 mg; once daily | 18 | 1.43; (1.30 to 1.56) | 1.16; (1.06 to 1.26) | 0.93; (0.85 to 1.01)
 |  |  | (reference arm for comparison was 25-mg-once-daily rilpivirine administered alone)
Rifampin; 600 mg once daily | 150 mg; once dailya | 16 | 0.31; (0.27 to 0.36) | 0.20; (0.18 to 0.23) | 0.11; (0.10 to 0.13)
Sildenafil; 50 mg single dose | 75 mg; once dailya | 16 | 0.92; (0.85 to 0.99) | 0.98; (0.92 to 1.05) | 1.04; (0.98 to 1.09)
Simeprevir; 150 mg once daily | 25 mg; once daily | 23 | 1.04; (0.95 to 1.13) | 1.12; (1.05 to 1.19) | 1.25; (1.16 to 1.35)
n = Maximum number of subjects with data; NA = Not available; ↔ = No change.
a This interaction study has been performed with a dose higher than the recommended dose for rilpivirine (25 mg once daily) assessing the maximal effect on the coadministered drug.
b Comparison based on historic controls.

12.4 Microbiology

Mechanism of Action

Dolutegravir inhibits HIV integrase by binding to the integrase active site and blocking the strand transfer step of retroviral DNA integration which is essential for the HIV replication cycle. Strand transfer biochemical assays using purified HIV-1 integrase and pre-processed substrate DNA resulted in IC50 values of 2.7 nM and 12.6 nM.

Rilpivirine is a diarylpyrimidine NNRTI of HIV-1 and inhibits HIV-1 replication by non-competitive inhibition of HIV-1 reverse transcriptase (RT). Rilpivirine does not inhibit the human cellular DNA polymerases α, β, and γ.

Antiviral Activity in Cell Culture

Dolutegravir exhibited antiviral activity against laboratory strains of wild-type HIV-1 with mean EC50 values of 0.5 nM to 2.1 nM (0.21 to 0.85 ng/mL) in peripheral blood mononuclear cells (PBMCs) and MT-4 cells. Dolutegravir exhibited antiviral activity against 13 clinically diverse clade B isolates with a mean EC50 value of 0.52 nM in a viral integrase susceptibility assay using the integrase coding region from clinical isolates. Dolutegravir demonstrated antiviral activity in cell culture against a panel of HIV-1 clinical isolates (3 in each group of M [clades A, B, C, D, E, F, and G] and 3 in group O) with EC50 values ranging from 0.02 nM to 2.14 nM.

Rilpivirine exhibited activity against laboratory strains of wild-type HIV-1 in an acutely infected T-cell line with a median EC50 value for HIV-1IIIB of 0.73 nM (0.27 ng/mL). Rilpivirine demonstrated antiviral activity against a broad panel of HIV-1 group M (clades A, B, C, D, F, G, H) primary isolates with EC50 values ranging from 0.07 nM to 1.01 nM (0.03 to 0.37 ng/mL) and was less active against group O primary isolates with EC50 values ranging from 2.88 to 8.45 nM (1.06 to 3.10 ng/mL).

Antiviral Activity in Combination with Other Antiviral Agents

Neither dolutegravir nor rilpivirine were antagonistic to all tested anti-HIV agents or with each other when tested in combination.

Resistance

Cell Culture: Dolutegravir-resistant viruses were selected in cell culture starting from different wild-type HIV‑1 strains and clades. Amino acid substitutions E92Q, G118R, S153F or Y, G193E, or R263K emerged in different passages and conferred decreased susceptibility to dolutegravir of up to 4-fold.

Rilpivirine-resistant strains were selected in cell culture starting from wild-type HIV-1 of different origins and clades as well as NNRTI-resistant HIV-1. The frequently observed amino acid substitutions that emerged and conferred decreased phenotypic susceptibility to rilpivirine included: L100I; K101E; V106I and A; V108I; E138K and G, Q, R; V179F and I; Y181C and I; V189I; G190E; H221Y; F227C; and M230I and L.

Virologically Suppressed Subjects: In the pooled SWORD-1 and SWORD-2 trials, 12 subjects (7 in SWORD-1 and 5 in SWORD-2) had confirmed virologic failure (HIV-1 RNA greater than 200 copies/mL) while receiving dolutegravir plus rilpivirine at any time through Week 148. Ten of the confirmed virologic failures had post-baseline resistance data, with 6 isolates showing evidence of rilpivirine resistance, and 2 with evidence of dolutegravir resistance substitutions. Six isolates showed genotypic and/or phenotypic resistance to rilpivirine with emergent NNRTI-resistance substitutions E138E/A (rilpivirine 1.6-fold change), M230M/L (rilpivirine 2-fold change), L100L/I, K101Q and E138A (rilpivirine 4.1-fold change), K101K/E (rilpivirine 1.2-fold change), K101K/E, M230M/L (rilpivirine 2-fold change), and L100L/V/M, M230M/L (rilpivirine 31-fold change). In addition, 1 virologic failure subject had NNRTI-resistance substitutions K103N and V179I at Week 88 with rilpivirine phenotypic fold change of 5.2 but had no baseline sample.

One virologic failure isolate had emergent INSTI-resistance substitution V151V/I present post-baseline with baseline INSTI-resistance substitutions N155N/H and G163G/R (by exploratory HIV proviral DNA archive sequencing); no integrase phenotypic data were available for this isolate at virologic failure. One other subject had the dolutegravir-resistance substitution G193E at baseline and virologic failure, but no detectable phenotypic resistance (fold change = 1.02) at Week 24.

No resistance-associated substitutions were observed for the 2 subjects meeting confirmed virologic failure in the comparative current antiretroviral regimen arms at Week 48.

Cross-Resistance

Dolutegravir: The susceptibility of dolutegravir was tested against 60 INSTI-resistant site-directed mutant HIV-1 viruses (28 with single substitutions and 32 with 2 or more substitutions). The single INSTI-resistance substitutions T66K, I151L, and S153Y conferred a greater than 2-fold decrease in dolutegravir susceptibility (range: 2.3-fold to 3.6-fold from reference). Combinations of multiple substitutions T66K/L74M; E92Q/N155H; G140C/Q148R; G140S/Q148H, R or K; Q148R/N155H; T97A/G140S/Q148, and substitutions at E138/G140/Q148 showed a greater than 2-fold decrease in dolutegravir susceptibility (range: 2.5-fold to 21-fold from reference).

Rilpivirine: Considering all of the available cell culture and clinical data, any of the following amino acid substitutions, when present at baseline, are likely to decrease the antiviral activity of rilpivirine: K101E or P; E138A, G, K, R, or Q; V179L; Y181C, I, or V; Y188L; H221Y; F227C; M230I or L.

Cross-resistance in site-directed mutant virus has been observed among NNRTIs. The single NNRTI substitutions K101P, Y181I, and Y181V conferred 52 times, 15 times, and 12 times decreased susceptibility to rilpivirine, respectively. The combination of E138K and M184I showed 6.7 times reduced susceptibility to rilpivirine compared with 2.8 times for E138K alone. The K103N substitution did not show reduced susceptibility to rilpivirine by itself. However, the combination of K103N and L100I resulted in a 7 times reduced susceptibility to rilpivirine. In another study, the Y188L substitution resulted in a reduced susceptibility to rilpivirine of 9 times for clinical isolates and 6 times for site-directed mutants. Combinations of 2 or 3 NNRTI resistance-associated substitutions gave decreased susceptibility to rilpivirine (fold-change range: 3.7 to 554) in 38% and 66% of mutants, respectively.

Cross-resistance to efavirenz, etravirine, and/or nevirapine is likely after virologic failure and development of rilpivirine resistance.

13 NONCLINICAL TOXICOLOGY

13.1 Carcinogenesis, Mutagenesis, Impairment of Fertility

Carcinogenesis

Two-year carcinogenicity studies in mice and rats were conducted with dolutegravir. Mice were administered doses of up to 500 mg/kg and rats were administered doses of up to 50 mg/kg. In mice, no significant increases in the incidence of drug-related neoplasms were observed at the highest doses tested, resulting in dolutegravir AUC exposures approximately 20 times higher than those in humans at the recommended dose of 50 mg once daily. In rats, no increases in the incidence of drug-related neoplasms were observed at the highest dose tested, resulting in dolutegravir AUC exposures approximately 17 times higher than those in humans at the recommended dose of 50 mg once daily.

Rilpivirine was evaluated for carcinogenic potential by oral gavage administration to mice and rats up to 104 weeks. Daily doses of 20, 60, and 160 mg/kg/day were administered to mice and doses of 40, 200, 500, and 1,500 mg/kg/day were administered to rats. In rats, there were no drug-related neoplasms. In mice, rilpivirine was positive for hepatocellular neoplasms in both males and females. The observed hepatocellular findings in mice may be rodent specific. At the lowest tested doses in the carcinogenicity studies, the systemic exposures (based on AUC) to rilpivirine were 21 (mice) and 3 (rats) times higher than those observed in humans at the recommended dose (25 mg once daily).

Mutagenesis

Dolutegravir was not genotoxic in the bacterial reverse mutation assay, mouse lymphoma assay, or in the in vivo rodent micronucleus assay.

Rilpivirine tested negative in the absence and presence of a metabolic activation system in the in vitro Ames reverse mutation assay and the in vitro clastogenicity mouse lymphoma assay. Rilpivirine did not induce chromosomal damage in the in vivo micronucleus test in mice.

Impairment of Fertility

Dolutegravir did not affect male or female fertility in rats at doses associated with exposures approximately 33 times higher than the exposures in humans at the doses of 50 mg once daily.

No human data on the effect of rilpivirine on fertility are available. In a study conducted in rats, there were no effects on mating or fertility with rilpivirine up to 400 mg/kg/day, a dose of rilpivirine that showed maternal toxicity. This dose is associated with an exposure that is approximately 40 times higher than the exposure in humans at the recommended dose of 25 mg once daily.

14 CLINICAL STUDIES

14.1 Clinical Trials in Adult Subjects Switching to JULUCA

The efficacy of JULUCA is supported by data from 2 open-label, controlled trials (SWORD-1 [NCT02429791] and SWORD-2 [NCT02422797]) in virologically suppressed patients switching from their current antiretroviral regimen to dolutegravir plus rilpivirine.

SWORD-1 and SWORD-2 are identical 148-week, Phase 3, randomized, multicenter, parallel-group, non-inferiority trials. A total of 1,024 adult HIV-1–infected subjects who were on a stable suppressive antiretroviral regimen (containing 2 NRTIs plus either an INSTI, an NNRTI, or a PI) for at least 6 months (HIV-1 RNA less than 50 copies/mL), with no history of treatment failure and no known substitutions associated with resistance to dolutegravir or rilpivirine received treatment in the trials. Subjects were randomized 1:1 to continue their current antiretroviral regimen (n = 511) or be switched to dolutegravir plus rilpivirine administered once daily (n = 513). Subjects originally assigned to continue their current antiretroviral regimen and who remained virologically suppressed at Week 48 switched to dolutegravir plus rilpivirine at Week 52 (n = 477).

The primary efficacy endpoint for the SWORD trials was the proportion of subjects with plasma HIV-1 RNA less than 50 copies/mL at Week 48.

At baseline, in the pooled analysis, the median age of subjects was 43 years (range: 21 to 79), 22% female, 20% non-white, 11% were CDC Class C (AIDS), and 11% had CD4+ cell count less than 350 cells/mm^3; these characteristics were similar between treatment arms. In the pooled analysis, 54%, 26%, and 20% of subjects were receiving an NNRTI, PI, or INSTI, respectively, as their baseline third-treatment-agent class prior to randomization. This distribution was similar between treatment arms.

The primary endpoint and other outcomes (including outcomes by key baseline covariates) for the pooled SWORD-1 and SWORD-2 trials are shown in Table 12. The virologic outcome results for SWORD-1 and SWORD-2 were similar to the pooled SWORD-1 and SWORD-2 virologic outcome results.

Table 12. Pooled Virologic Outcomes of Randomized Treatment in SWORD-1 and SWORD-2 Trials at Week 48 in Virologically Suppressed Subjects Who Switched to JULUCA (Snapshot Algorithm)
 | Pooled Data
 | Dolutegravir plus Rilpivirine; (n = 513) | Current Antiretroviral Regimen; (n = 511)
HIV-1 RNA <50 copies/mL | 95% | 95%
Treatment Difference | -0.2%; (95% CI: -3.0%, 2.5%)
HIV-1 RNA ≥50 copies/mL | <1% | 1%
Treatment Difference | -0.6%; (95% CI: -1.7%, 0.6%)
Data in window not <50 copies/mL | 0 | <1%
Discontinued for lack of efficacy | <1% | <1%
Discontinued for other reasons while not <50 copies/mL | <1% | <1%
Change in ART | 0 | <1%
No virologic data at Week 48 window | 5% | 4%
Discontinued due to adverse event or death | 3% | <1%
Discontinued for other reasonsa | 1% | 3%
Missing data during window but on study | 0 | <1%
Proportion (%) of Subjects with HIV-1 RNA <50 copies/mL by Baseline Category
Baseline CD4+ (cells/mm^3)
<350 | 88% (n = 58) | 88% (n = 52)
≥350 | 96% (n = 455) | 96% (n = 459)
Baseline Third-Treatment-Agent Class
INSTI | 94% (n = 105) | 95% (n = 97)
NNRTI | 96% (n = 275) | 95% (n = 278)
PI | 93% (n = 133) | 94% (n = 136)
Gender
Male | 95% (n = 393) | 96% (n = 403)
Female | 93% (n = 120) | 91% (n = 108)
Race
White | 94% (n = 421) | 95% (n = 400)
African-America/African Heritage/Other | 99% (n = 92) | 95% (n = 111)
Age (years)
<50 | 96% (n = 366) | 94% (n = 369)
≥50 | 93% (n = 147) | 96% (n = 142)
INSTI = Integrase strand transfer inhibitor; NNRTI = Non-nucleoside reverse transcriptase inhibitor; PI = Protease inhibitor.
a Other includes reasons such as withdrew consent, loss to follow-up, moved, and protocol deviation.

Treatment differences were maintained across baseline characteristics including, CD4+ cell count, age, gender, race, and baseline third-treatment-agent class.

At Week 148 in the pooled SWORD-1 and SWORD-2 trials, 84% of subjects who received dolutegravir plus rilpivirine from study start had plasma HIV-1 RNA less than 50 copies/mL (Snapshot algorithm). In subjects who initially remained on their current antiretroviral regimen and switched to dolutegravir plus rilpivirine at Week 52, 90% had plasma HIV-1 RNA less than 50 copies/mL at Week 148 (Snapshot algorithm), which was comparable to the response rate (89%) observed at Week 100 (similar exposure duration) in subjects receiving dolutegravir plus rilpivirine from study start.

16 HOW SUPPLIED/STORAGE AND HANDLING

Each JULUCA tablet contains 50 mg of dolutegravir and 25 mg of rilpivirine, and is a pink, oval, film-coated, biconvex tablet debossed with “SV J3T” on one side.

Bottle of 30 tablets with child-resistant closure (contains a desiccant) NDC 49702-242-13.

Store and dispense in the original package, protect from moisture, and keep the bottle tightly closed. Do not remove desiccant.

Store at 20°C to 25°C (68°F to 77°F); excursions permitted between 15°C and 30°C (59°F and 86°F) [See USP Controlled Room Temperature].

17 PATIENT COUNSELING INFORMATION

Advise the patient to read the FDA-approved patient labeling (Patient Information).

Severe Skin and Hypersensitivity Reactions

Advise patients to immediately contact their healthcare provider if they develop a rash. Instruct patients to immediately stop taking JULUCA and seek medical attention if they develop a rash associated with any of the following symptoms, as it may be a sign of a more serious reaction such as DRESS severe hypersensitivity: fever; generally ill feeling; extreme tiredness; muscle or joint aches; blisters or peeling of the skin; oral blisters or lesions; eye inflammation; facial swelling; swelling of the eyes, lips, tongue, or mouth; breathing difficulty; and/or signs and symptoms of liver problems (e.g., yellowing of the skin or whites of the eyes; dark or tea-colored urine; pale-colored stools or bowel movements; nausea; vomiting; loss of appetite; or pain, aching, or sensitivity on the right side below the ribs). Advise patients that if hypersensitivity occurs, they will be closely monitored, laboratory tests will be ordered, and appropriate therapy will be initiated [see Warnings and Precautions (5.1)].

Hepatotoxicity

Inform patients that hepatotoxicity has been reported with rilpivirine and dolutegravir, components of JULUCA [see Warnings and Precautions (5.2), Adverse Reactions (6.1)]. Inform patients that monitoring for hepatotoxicity is recommended.

Depressive Disorders

Inform patients that depressive disorders (depressed mood, depression, dysphoria, major depression, mood altered, negative thoughts, suicide attempt, suicidal ideation) have been reported with the components of JULUCA. Advise patients to seek immediate medical evaluation if they experience depressive symptoms [see Warnings and Precautions (5.3), Adverse Reactions (6.1)].

Drug Interactions

JULUCA may interact with many drugs; therefore, advise patients to report to their healthcare provider the use of any other prescription or nonprescription medication or herbal products including St. John’s wort [see Contraindications (4), Warnings and Precautions (5.4), Drug Interactions (7)].

Administration Instruction

Inform patients that it is important to take JULUCA once daily on a regular dosing schedule with a meal and to avoid missing doses as it can result in development of resistance. Instruct patients that if they miss a dose of JULUCA, to take it as soon as they remember with a meal. Advise patients not to double their next dose. Advise the patient a protein drink alone does not replace a meal [see Clinical Pharmacology (12.3)].

Pregnancy Registry

Inform patients that there is an antiretroviral pregnancy registry to monitor fetal outcomes in those exposed to JULUCA during pregnancy [see Use in Specific Populations (8.1)].

Lactation

Inform individuals with HIV-1 infection that the potential risks of breastfeeding include: (1) HIV-1 transmission (in HIV-1–negative infants), (2) developing viral resistance (in HIV-1–positive infants), and (3) adverse reactions in a breastfed infant similar to those seen in adults [see Use in Specific Populations (8.2)].

Storage

Instruct patients to store JULUCA in the original bottle to protect from moisture and keep the bottle tightly closed. Do not remove desiccant [see How Supplied/Storage and Handling (16)].

JULUCA, TIVICAY, and TRIUMEQ are trademarks owned by or licensed to the ViiV Healthcare group of companies.

The other brand listed is a trademark owned by or licensed to its respective owner and is not a trademark owned by or licensed to the ViiV Healthcare group of companies. The maker of this brand is not affiliated with and does not endorse the ViiV Healthcare group of companies or its products.

Manufactured for:

ViiV Healthcare
Durham, NC 27701

©2025 ViiV Healthcare group of companies or its licensor.

JLC:11PI

PATIENT INFORMATION

_ _ _ _ _ _ _ _ _ _ _ _ _ _ _ _ _ _ _ _ _ _ _ _ _ _ _ _ _ _ _ _ _ _ _ _ _ _ _ _ _ _ __ _ _ _ _ _ _ _ _

PATIENT INFORMATION

JULUCA (Jah-LOO-kah)

(dolutegravir and rilpivirine tablets)

What is JULUCA?

JULUCA is a prescription medicine that is used without other antiretroviral medicines to treat Human Immunodeficiency Virus-1 (HIV-1) infection in adults to replace their current HIV-1 medicines when their healthcare provider determines that they meet certain requirements.

HIV-1 is the virus that causes Acquired Immune Deficiency Syndrome (AIDS).

It is not known if JULUCA is safe and effective in children.

Do not take JULUCA if you:

- have ever had an allergic reaction to a medicine that contains dolutegravir or rilpivirine.
- are taking any of the following medicines:

- dofetilide
- carbamazepine
- oxcarbazepine
- phenobarbital
- phenytoin
- rifampin
- rifapentine

- proton pump inhibitors, including:
  - esomeprazole
  - lansoprazole
  - omeprazole
  - pantoprazole sodium
  - rabeprazole
- St. John's wort (Hypericum perforatum)
- more than 1 dose of the steroid medicine dexamethasone or dexamethasone sodium phosphate

Before you take JULUCA, tell your healthcare provider about all of your medical conditions, including if you:

- have ever had a severe skin rash or an allergic reaction to medicines that contain dolutegravir or rilpivirine.
- have or have had liver problems, including hepatitis B or C infection.
- have ever had a mental health problem.
- are pregnant or plan to become pregnant. Talk to your healthcare provider about the benefits and risks of treatment with JULUCA during pregnancy.

Pregnancy Registry. There is a pregnancy registry for those who take JULUCA during pregnancy. The purpose of this registry is to collect information about the health of you and your baby. Talk with your healthcare provider about how you can take part in this registry.

- are breastfeeding or plan to breastfeed. One of the medicines in JULUCA passes to your baby in your breast milk. Talk with your healthcare provider about the following risks to your baby from breastfeeding during treatment with JULUCA:
  - the HIV-1 virus may pass to your baby if your baby does not have HIV-1 infection.
  - the HIV-1 virus may become harder to treat if your baby has HIV-1 infection.
  - your baby may get side effects from JULUCA.

Tell your healthcare provider about all the medicines you take, including prescription and over-the-counter medicines, vitamins, and herbal supplements.

Some medicines interact with JULUCA. Keep a list of your medicines and show it to your healthcare provider and pharmacist when you get a new medicine.

- You can ask your healthcare provider or pharmacist for a list of medicines that interact with JULUCA.
- Do not start taking a new medicine without telling your healthcare provider. Your healthcare provider can tell you if it is safe to take JULUCA with other medicines.

How should I take JULUCA?

- Take JULUCA 1 time a day exactly as your healthcare provider tells you.
- Always take JULUCA with a meal. A protein drink alone does not replace a meal.
- Do not change your dose or stop taking JULUCA without talking with your healthcare provider.
- If you take an H2-receptor antagonist (famotidine, cimetidine, nizatidine, or ranitidine), JULUCA should be taken at least 4 hours before or 12 hours after you take these medicines.
- If you take antacids, laxatives, or other products that contain aluminum, calcium carbonate, magnesium, or buffered medicines, JULUCA should be taken at least 4 hours before or 6 hours after you take these medicines.
If you need to take iron or calcium supplements by mouth during treatment with JULUCA:
  1. You may take these supplements at the same time that you take JULUCA with food.
  2. If you do not take these supplements with JULUCA and food, take JULUCA at least 4 hours before or 6 hours after you take these supplements.
- Do not miss a dose of JULUCA.
- If you miss a dose of JULUCA, take it as soon as you remember with a meal. Do not take 2 doses at the same time.
- Stay under the care of a healthcare provider during treatment with JULUCA.
- Do not run out of JULUCA. The virus in your blood may increase and the virus may become harder to treat. When your supply starts to run low, get more from your healthcare provider or pharmacy.
- If you take too much JULUCA, call your healthcare provider or go to the nearest hospital emergency room right away.

What are the possible side effects of JULUCA?

JULUCA can cause serious side effects, including:

- Severe skin rash and allergic reactions. Call your healthcare provider right away if you develop a rash with JULUCA. Stop taking JULUCA and get medical help right away if you develop a rash with any of the following signs or symptoms:

- fever
- generally ill feeling
- tiredness
- muscle or joint aches
- blisters or sores in mouth

- blisters or peeling of the skin
- redness or swelling of the eyes
- swelling of the mouth, face, lips, or tongue
- problems breathing

- Liver problems. People with a history of hepatitis B or C virus who have certain liver function test changes may have an increased risk of developing new or worsening changes in certain liver tests during treatment with JULUCA. Liver problems, including liver failure, have also happened in people without history of liver disease or other risk factors. Your healthcare provider may do blood tests to check your liver function. Call your healthcare provider right away if you develop any of the following signs or symptoms of liver problems:

- your skin or the white part of your eyes turns yellow (jaundice)
- dark or “tea-colored” urine
- light-colored stools (bowel movements)

- nausea or vomiting
- loss of appetite
- pain, aching, or tenderness on the right side of your stomach area

- Depression or mood changes. Tell your healthcare provider right away or get medical help if you have any of the following symptoms:
  - feeling sad or hopeless
  - feeling anxious or restless
  - have thoughts of hurting yourself (suicide) or have tried to hurt yourself
- The most common side effects of JULUCA include:

- diarrhea
- nausea

- headache

These are not all the possible side effects of JULUCA. For more information, ask your healthcare provider or pharmacist. Call your doctor for medical advice about side effects.

You may report side effects to FDA at 1‑800‑FDA‑1088.

How should I store JULUCA?

- Store JULUCA at room temperature between 68°F to 77°F (20°C to 25°C).
- Store JULUCA tablets in the original bottle. Keep the bottle tightly closed and protected from moisture.
- The bottle of JULUCA contains a desiccant to help keep your medicine dry (protect it from moisture). Keep the desiccant in the bottle. Do not remove the desiccant.

Keep JULUCA and all medicines out of the reach of children.

General information about the safe and effective use of JULUCA.

Medicines are sometimes prescribed for purposes other than those listed in a Patient Information leaflet. Do not use JULUCA for a condition for which it was not prescribed. Do not give JULUCA to other people, even if they have the same symptoms that you have. It may harm them. You can ask your healthcare provider or pharmacist for information about JULUCA that is written for health professionals.

What are the ingredients in JULUCA?

Active ingredients: dolutegravir and rilpivirine.
Inactive ingredients: croscarmellose sodium, D-mannitol, lactose monohydrate, magnesium stearate, microcrystalline cellulose, polysorbate 20, povidone K29/32 and K30, silicified microcrystalline cellulose, sodium starch glycolate, and sodium stearyl fumarate.
The tablet film-coating contains: iron oxide red, iron oxide yellow, macrogol/PEG, polyvinyl alcohol-part hydrolyzed, talc, and titanium dioxide.

Manufactured for:

ViiV Healthcare
Durham, NC 27701

Trademarks are owned by or licensed to the ViiV Healthcare group of companies.

©2025 ViiV Healthcare group of companies or its licensor.
JLC:10PIL
For more information go to www.JULUCA.com or call 1-877-844-8872.

This Patient Information has been approved by the U.S. Food and Drug Administration. Revised: 11/2025

PACKAGE LABEL

PRINCIPAL DISPLAY PANEL

NDC 49702-242-13

Juluca

(dolutegravir and rilpivirine)

Tablets

50 mg/25 mg

Rx Only

Note to pharmacist: Do not cover ALERT box with pharmacy label.

ALERT: Find out about medicines that should NOT be taken with JULUCA.

30 tablets

Each film-coated tablet contains 50 mg of dolutegravir (equivalent to 52.6 mg dolutegravir sodium) and 25 mg of rilpivirine (equivalent to 27.5 mg rilpivirine hydrochloride).

Keep out of reach of children.

Store at 20ºC to 25ºC (68ºF to 77ºF); excursions permitted between 15ºC and 30ºC (59ºF and 86ºF) [see USP Controlled Room Temperature].

Store and dispense in the original package, protect from moisture, and keep the bottle tightly closed. Do not remove desiccant.

See prescribing information for dosage information.

Do not accept if membrane seal under cap is missing or broken

Mfd for:

ViiV Healthcare

Durham, NC 27701

by:

GlaxoSmithKline, Durham NC 27701

Trademarks owned or licensed by ViiV Healthcare.

©2024 ViiV Healthcare or licensor.

Made in Spain

Rev. 12/24

A094954 (62000000094954)